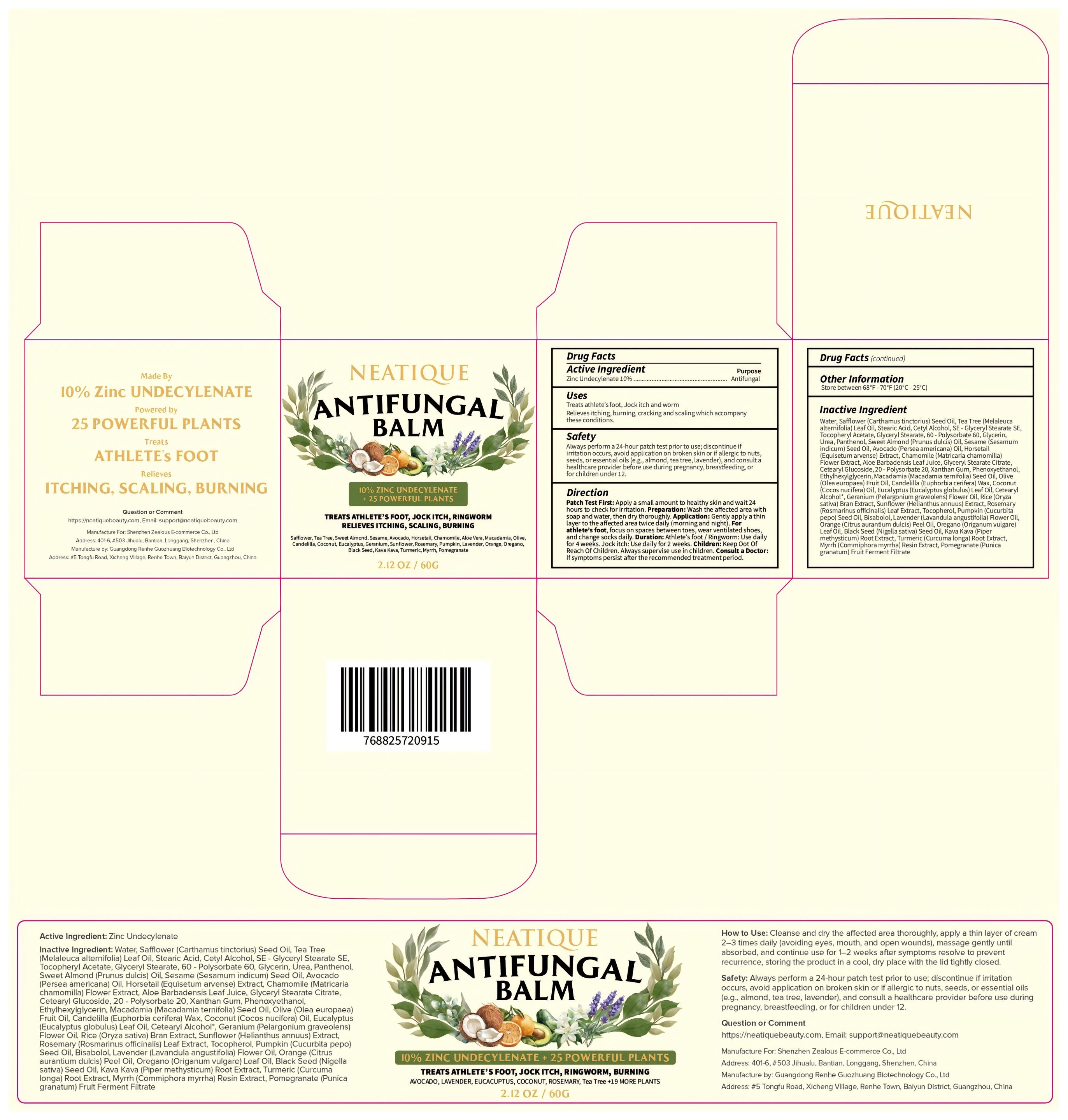 DRUG LABEL: Neatique Antifungal Balm
NDC: 85587-001 | Form: CREAM
Manufacturer: Shenzhen Zealous Ecommerce Technology Co., Ltd
Category: otc | Type: HUMAN OTC DRUG LABEL
Date: 20250423

ACTIVE INGREDIENTS: ZINC UNDECYLENATE 10 g/100 g
INACTIVE INGREDIENTS: BISABOLOL; LAVENDER OIL; ALOE BARBADENSIS LEAF JUICE; CURCUMA LONGA (TURMERIC) ROOT; STEARIC ACID; POLYSORBATE 60; OLEA EUROPAEA (OLIVE) FRUIT OIL; EUPHORBIA CERIFERA (CANDELILLA) WAX; MELALEUCA ALTERNIFOLIA (TEA TREE) LEAF OIL; .ALPHA.-TOCOPHEROL ACETATE; XANTHAN GUM; PHENOXYETHANOL; COCOS NUCIFERA (COCONUT) OIL; EUCALYPTUS GLOBULUS LEAF OIL; PUMPKIN SEED OIL; CITRUS AURANTIUM DULCIS (ORANGE) PEEL OIL; COMMIPHORA AFRICANA RESIN; HYDROGENATED MACADAMIA SEED OIL; GERANIUM OIL, ALGERIAN TYPE; CARTHAMUS TINCTORIUS (SAFFLOWER) SEED OIL; CETYL ALCOHOL; GLYCERYL STEARATE SE; GLYCERIN; UREA; SESAMUM INDICUM (SESAME) SEED OIL; EQUISETUM ARVENSE TOP; ETHYLHEXYLGLYCERIN; ROSMARINUS OFFICINALIS (ROSEMARY) LEAF OIL; TOCOPHEROL; POMEGRANATE; POLYSORBATE 20; CHAMOMILE; OREGANO LEAF OIL; WATER; ALMOND OIL; PERSEA GRATISSIMA (AVOCADO) OIL; PANTHENOL; NIGELLA SATIVA SEED OIL; PIPER METHYSTICUM ROOT

85587-001

Active Ingredient

Zinc Undecylenate 10%

Purpose

Treats athlete’s foot, Jock itch and worm, Relieves itching, burning, cracking and scaling which accompany these conditions.

Use

Apply a small amount to healthy skin and wait 24 hours to check for irritation

Warnings

Always perform a 24-hour patch test prior to use; discontinue if irritation occurs, avoid application on broken skin or if allergic to nuts, seeds, or essential oils (e.g., almond, tea tree, lavender), and consult a healthcare provider before use during pregnancy, breastfeeding, or for children under 12.

Do not use

Avoid application on broken skin or if allergic to nuts, seeds, or essential oils

When Using

Wash the affected area with soap and water, then dry thoroughly.

Stop Use

Discontinue if irritation occurs

Ask Doctor

Consult a healthcare provider before use during pregnancy, breastfeeding, or for children under 12.

Keep Out Of Reach Of Children

Directions

Gently apply a thin layer to the affected area twice daily (morning and night).

Other information

Store between 68°F - 77°F (20°C - 25°C)

Inactive ingredients

Water,Safflower (Carthamus tinctorius) Seed Oil, Tea Tree (Melaleuca alternifolia) Leaf Oil, Stearic Acid, Cetyl Alcohol, SE - Glyceryl Stearate SE, Tocopheryl Acetate, Glyceryl Stearate, 60 - Polysorbate 60, Glycerin, Urea, Panthenol, Sweet Almond (Prunus dulcis) Oil, Sesame (Sesamum indicum) Seed Oil, Avocado (Persea americana) Oil, Horsetail (Equisetum arvense) Extract, Chamomile (Matricaria chamomilla) Flower Extract, Aloe Barbadensis Leaf Juice, Glyceryl Stearate Citrate, Cetearyl Glucoside, 20 - Polysorbate 20, Xanthan Gum, Phenoxyethanol, Ethylhexylglycerin, Macadamia (Macadamia ternifolia) Seed Oil, Olive (Olea europaea) Fruit Oil, Candelilla (Euphorbia cerifera) Wax, Coconut (Cocos nucifera) Oil, Eucalyptus (Eucalyptus globulus) Leaf Oil, Cetearyl Alcohol*, Geranium (Pelargonium graveolens) Flower Oil, Rice (Oryza sativa) Bran Extract, Sunflower (Helianthus annuus) Extract, Rosemary (Rosmarinus officinalis) Leaf Extract, Tocopherol, Pumpkin (Cucurbita pepo) Seed Oil, Bisabolol, Lavender (Lavandula angustifolia) Flower Oil, Orange (Citrus aurantium dulcis) Peel Oil, Oregano (Origanum vulgare) Leaf Oil, Black Seed (Nigella sativa) Seed Oil, Kava Kava (Piper methysticum) Root Extract, Turmeric (Curcuma longa) Root Extract, Myrrh (Commiphora myrrha) Resin Extract, Pomegranate (Punica granatum) Fruit Ferment Filtrate

Questions

https://neatiquebeauty.com

Email: support@neatiquebeauty.com